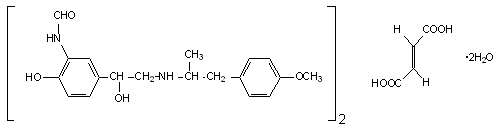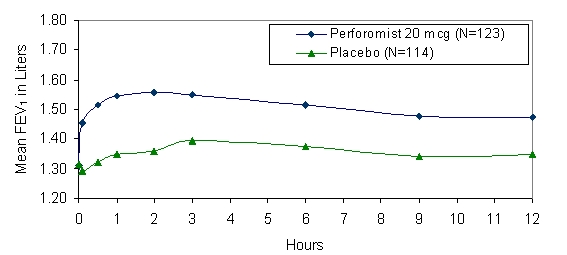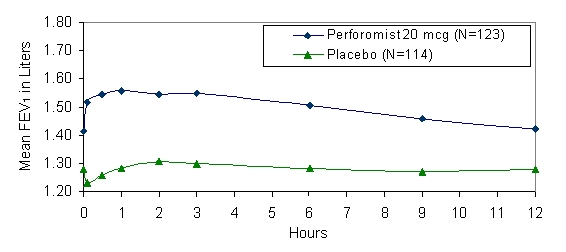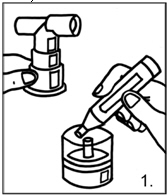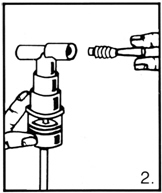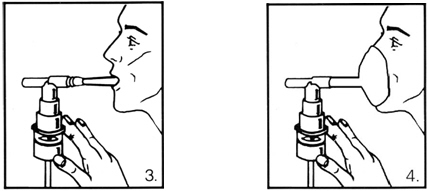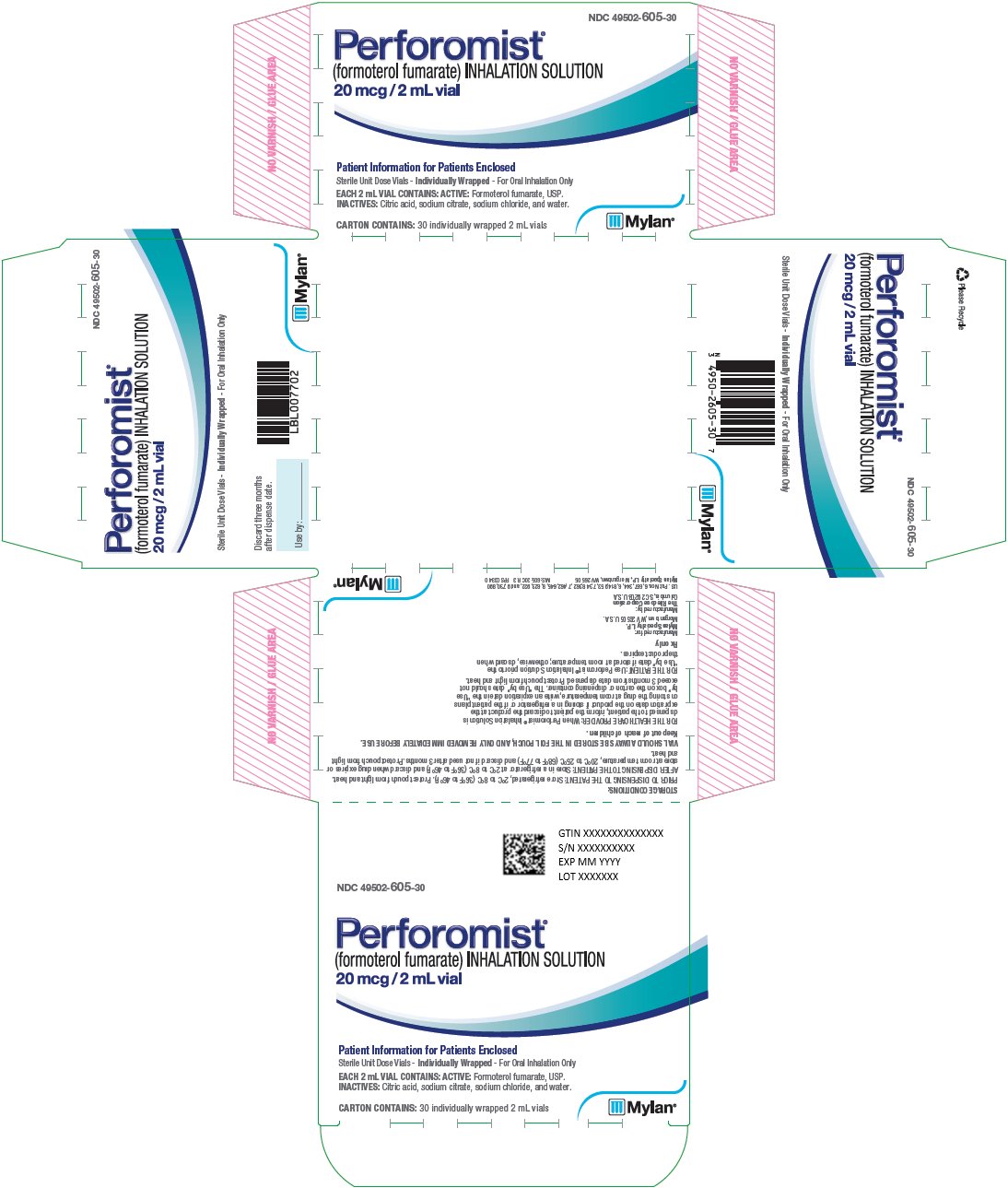 DRUG LABEL: Perforomist
NDC: 49502-605 | Form: SOLUTION
Manufacturer: Viatris Specialty LLC
Category: prescription | Type: HUMAN PRESCRIPTION DRUG LABEL
Date: 20190531

ACTIVE INGREDIENTS: FORMOTEROL FUMARATE 20 ug/2 mL
INACTIVE INGREDIENTS: SODIUM CHLORIDE; CITRIC ACID MONOHYDRATE; TRISODIUM CITRATE DIHYDRATE; WATER

HIGHLIGHTS OF PRESCRIBING INFORMATION

These highlights do not include all the information needed to use PERFOROMIST INHALATION SOLUTION safely and effectively. See full prescribing information for PERFOROMIST INHALATION SOLUTION.
PERFOROMIST® (formoterol fumarate) Inhalation Solution
Initial U.S. Approval: 2001

RECENT MAJOR CHANGES

Boxed Warning Removed-5/2019

Contraindications, revised (4) 5/2019

Warnings and Precautions, revised 5/2019

Serious Asthma-Related Events – Hospitalizations, Intubations, Death (5.1) 5/2019

1 INDICATIONS AND USAGE

PERFOROMIST Inhalation Solution is a long-acting beta2-adrenergic agonist (beta2-agonist) indicated for:

- Long-term, twice daily (morning and evening) administration in the maintenance treatment of bronchoconstriction in patients with chronic obstructive pulmonary disease (COPD), including chronic bronchitis and emphysema. (1.1)

Important limitations of use:

- PERFOROMIST Inhalation Solution is not indicated to treat acute deteriorations of chronic obstructive pulmonary disease. (1.2, 5.2)
- PERFOROMIST Inhalation Solution is not indicated to treat asthma. (1.2)

2 DOSAGE AND ADMINISTRATION

For oral inhalation only.

- One 20 mcg/2 mL vial every 12 hours (2)
- For use with a standard jet nebulizer (with a facemask or mouthpiece) connected to an air compressor (2)

3 DOSAGE FORMS AND STRENGTHS

Inhalation Solution (unit dose vial for nebulization); 20 mcg/2 mL solution (3)

4 CONTRAINDICATIONS

- Use of a LABA, including PERFOROMIST, without an inhaled corticosteroid is contraindicated in patients with asthma. (4)

5 WARNINGS AND PRECAUTIONS

- LABA as monotherapy (without inhaled corticosteroid) for asthma increases the risk of serious asthma-related events. (5.1)
- Do not initiate PERFOROMIST Inhalation Solution in acutely deteriorating patients. (5.2)
- Do not use for relief of acute symptoms. Concomitant short-acting beta2-agonists can be used as needed for acute relief. (5.2)
- Do not exceed the recommended dose. Excessive use of PERFOROMIST Inhalation Solution or use in conjunction with other medications containing long-acting beta2-agonists, can result in clinically significant cardiovascular effects, and may be fatal. (5.3, 5.5)
- Life-threatening paradoxical bronchospasm can occur. Discontinue PERFOROMIST Inhalation Solution immediately. (5.4)
- Use with caution in patients with cardiovascular or convulsive disorders, thyrotoxicosis, or with sensitivity to sympathomimetic drugs. (5.6, 5.7)

6 ADVERSE REACTIONS

Most common adverse reactions (>2% and more common than placebo) are diarrhea, nausea, nasopharyngitis, dry mouth, vomiting, dizziness, and insomnia (6.2)

To report SUSPECTED ADVERSE REACTIONS, contact Mylan at 1-877-446-3679 (1-877-4-INFO-RX) or FDA at 1-800-FDA-1088 or www.fda.gov/medwatch.

7 DRUG INTERACTIONS

- Other adrenergic drugs may potentiate effect. Use with caution. (5.3, 7.1)
- Xanthine derivatives, steroids, diuretics, or non-potassium sparing diuretics may potentiate hypokalemia or ECG changes. Use with caution. (5.7, 7.2, 7.3)
- MAO inhibitors, tricyclic antidepressants and drugs that prolong QTc interval may potentiate effect on the cardiovascular system. Use with extreme caution. (7.4)
- Beta-blockers may decrease effectiveness. Use with caution and only when medically necessary. (7.5)

FULL PRESCRIBING INFORMATION

1 INDICATIONS AND USAGE

1.1 Maintenance Treatment of COPD

PERFOROMIST (formoterol fumarate) Inhalation Solution is indicated for the long-term, twice daily (morning and evening) administration in the maintenance treatment of bronchoconstriction in patients with chronic obstructive pulmonary disease (COPD), including chronic bronchitis and emphysema.

1.2 Important Limitations of Use

PERFOROMIST Inhalation Solution is not indicated to treat acute deteriorations of chronic obstructive pulmonary disease [see WARNINGS AND PRECAUTIONS (5.2)].

PERFOROMIST Inhalation Solution is not indicated to treat asthma. The safety and effectiveness of PERFOROMIST Inhalation Solution in asthma have not been established.

2 DOSAGE AND ADMINISTRATION

The recommended dose of PERFOROMIST (formoterol fumarate) Inhalation Solution is one 20 mcg unit-dose vial administered twice daily (morning and evening) by nebulization. A total daily dose greater than 40 mcg is not recommended.

PERFOROMIST Inhalation Solution should be administered by the orally inhaled route via a standard jet nebulizer connected to an air compressor. The safety and efficacy of PERFOROMIST Inhalation Solution have been established in clinical trials when administered using the PARI-LC Plus® nebulizer (with a facemask or mouthpiece) and the PRONEB® Ultra compressor. The safety and efficacy of PERFOROMIST Inhalation Solution delivered from non-compressor based nebulizer systems have not been established.

PERFOROMIST Inhalation Solution should always be stored in the foil pouch, and only removed IMMEDIATELY BEFORE USE. Contents of any partially used container should be discarded.

If the recommended maintenance treatment regimen fails to provide the usual response, medical advice should be sought immediately, as this is often a sign of destabilization of COPD. Under these circumstances, the therapeutic regimen should be re-evaluated and additional therapeutic options should be considered.

The drug compatibility (physical and chemical), efficacy, and safety of PERFOROMIST Inhalation Solution when mixed with other drugs in a nebulizer have not been established.

3 DOSAGE FORMS AND STRENGTHS

PERFOROMIST (formoterol fumarate) Inhalation Solution is supplied as a sterile solution for nebulization in low-density polyethylene unit-dose vials. Each vial contains formoterol fumarate dihydrate, USP equivalent to 20 mcg/2 mL of formoterol fumarate.

4 CONTRAINDICATIONS

Use of a LABA, including PERFOROMIST, without an inhaled corticosteroid is contraindicated in patients with asthma [see WARNINGS and PRECAUTIONS (5.1)]. PERFOROMIST is not indicated for the treatment of asthma.

5 WARNINGS AND PRECAUTIONS

5.1 Serious Asthma-Related Events – Hospitalizations, Intubations, Death

- The safety and efficacy of PERFOROMIST in patients with asthma have not been established. PERFOROMIST is not indicated for the treatment of asthma [see CONTRAINDICATIONS (4)].
- Use of long-acting beta2-adrenergic agonists (LABA) as monotherapy [without inhaled corticosteroids (ICS)] for asthma is associated with an increased risk of asthma-related death. Available data from controlled clinical trials also suggest that use of LABA as monotherapy increases the risk of asthma-related hospitalization in pediatric and adolescent patients. These findings are considered a class effect of LABA monotherapy. When LABA are used in fixed‑dose combination with ICS, data from large clinical trials do not show a significant increase in the risk of serious asthma-related events (hospitalizations, intubations, death) compared with ICS alone.
  - A 28-week, placebo-controlled US study comparing the safety of another LABA (salmeterol) with placebo, each added to usual asthma therapy, showed an increase in asthma-related deaths in patients receiving salmeterol (13/13,176 in patients treated with salmeterol vs. 3/13,179 in patients treated with placebo; RR 4.37, 95% CI 1.25, 15.34). The increased risk of asthma-related death is considered a class effect of the long-acting beta2-adrenergic agonists, including PERFOROMIST Inhalation Solution.
  - No study adequate to determine whether the rate of asthma related death is increased in patients treated with PERFOROMIST Inhalation Solution has been conducted. Clinical studies with formoterol fumarate administered as a dry powder inhaler suggested a higher incidence of serious asthma exacerbations in patients who received formoterol than in those who received placebo. The sizes of these studies were not adequate to precisely quantify the differences in serious asthma exacerbation rates between treatment groups.
- Available data do not suggest an increased risk of death with use of LABA in patients with COPD.

5.2 Deterioration of Disease and Acute Episodes

PERFOROMIST Inhalation Solution should not be initiated in patients with acutely deteriorating COPD, which may be a life-threatening condition. PERFOROMIST Inhalation Solution has not been studied in patients with acutely deteriorating COPD. The use of PERFOROMIST Inhalation Solution in this setting is inappropriate.

PERFOROMIST Inhalation Solution should not be used for the relief of acute symptoms, i.e., as rescue therapy for the treatment of acute episodes of bronchospasm. PERFOROMIST Inhalation Solution has not been studied in the relief of acute symptoms and extra doses should not be used for that purpose. Acute symptoms should be treated with an inhaled short-acting beta2-agonist.

When beginning PERFOROMIST Inhalation Solution, patients who have been taking inhaled, short-acting beta2-agonists on a regular basis (e.g., four times a day) should be instructed to discontinue the regular use of these drugs and use them only for symptomatic relief of acute respiratory symptoms. When prescribing PERFOROMIST Inhalation Solution, the healthcare provider should also prescribe an inhaled, short-acting beta2-agonist and instruct the patient how it should be used. Increasing inhaled beta2-agonist use is a signal of deteriorating disease for which prompt medical attention is indicated. COPD may deteriorate acutely over a period of hours or chronically over several days or longer. If PERFOROMIST Inhalation Solution no longer controls the symptoms of bronchoconstriction, or the patient’s inhaled, short-acting beta2-agonist becomes less effective or the patient needs more inhalation of short-acting beta2-agonist than usual, these may be markers of deterioration of disease. In this setting, a re-evaluation of the patient and the COPD treatment regimen should be undertaken at once. Increasing the daily dosage of PERFOROMIST Inhalation Solution beyond the recommended 20 mcg twice daily dose is not appropriate in this situation.

5.3 Excessive Use and Use with Other Long-Acting Beta2-Agonists

As with other inhaled beta2-adrenergic drugs, PERFOROMIST Inhalation Solution should not be used more often, at higher doses than recommended, or in conjunction with other medications containing long-acting beta2-agonists, as an overdose may result. Clinically significant cardiovascular effects and fatalities have been reported in association with excessive use of inhaled sympathomimetic drugs.

5.4 Paradoxical Bronchospasm

As with other inhaled beta2-agonists, PERFOROMIST Inhalation Solution can produce paradoxical bronchospasm that may be life-threatening. If paradoxical bronchospasm occurs, PERFOROMIST Inhalation Solution should be discontinued immediately and alternative therapy instituted.

5.5 Cardiovascular Effects

PERFOROMIST Inhalation Solution, like other beta2-agonists, can produce a clinically significant cardiovascular effect in some patients as measured by increases in pulse rate, systolic and/or diastolic blood pressure, and/or symptoms. If such effects occur, PERFOROMIST Inhalation Solution may need to be discontinued. In addition, beta-agonists have been reported to produce ECG changes, such as flattening of the T wave, prolongation of the QTc interval, and ST segment depression. The clinical significance of these findings is unknown. Therefore, PERFOROMIST Inhalation Solution, like other sympathomimetic amines, should be used with caution in patients with cardiovascular disorders, especially coronary insufficiency, cardiac arrhythmias, and hypertension.

5.6 Coexisting Conditions

PERFOROMIST Inhalation Solution, like other sympathomimetic amines, should be used with caution in patients with convulsive disorders or thyrotoxicosis, and in patients who are unusually responsive to sympathomimetic amines. Doses of the related beta2-agonist albuterol, when administered intravenously, have been reported to aggravate preexisting diabetes mellitus and ketoacidosis.

5.7 Hypokalemia and Hyperglycemia

Beta-agonist medications may produce significant hypokalemia in some patients, possibly through intracellular shunting, which has the potential to produce adverse cardiovascular effects [see CLINICAL PHARMACOLOGY (12.2)]. The decrease in serum potassium is usually transient, not requiring supplementation. Beta-agonist medications may produce transient hyperglycemia in some patients.

Clinically significant changes in serum potassium and blood glucose were infrequent during clinical studies with long-term administration of PERFOROMIST Inhalation Solution at the recommended dose.

5.8 Immediate Hypersensitivity Reactions

Immediate hypersensitivity reactions may occur after administration of PERFOROMIST Inhalation Solution, as demonstrated by cases of anaphylactic reactions, urticaria, angioedema, rash, and bronchospasm.

6 ADVERSE REACTIONS

Long-acting beta2-adrenergic agonists, such as PERFOROMIST, as monotherapy (without an inhaled corticosteroid) for asthma increase the risk of asthma-related events. PERFOROMIST is not indicated for the treatment of asthma [see WARNINGS AND PRECAUTIONS (5.1)].

6.1 Beta2-Agonist Adverse Reaction Profile

Adverse reactions to PERFOROMIST Inhalation Solution are expected to be similar in nature to other beta2-adrenergic receptor agonists including: angina, hypertension or hypotension, tachycardia, arrhythmias, nervousness, headache, tremor, dry mouth, muscle cramps, palpitations, nausea, dizziness, fatigue, malaise, insomnia, hypokalemia, hyperglycemia, and metabolic acidosis.

6.2 Clinical Trials Experience

Because clinical trials are conducted under widely varying conditions, adverse reaction rates observed in the clinical trials of a drug cannot be directly compared to rates in the clinical trials of another drug and may not reflect the rates observed in practice.

Adults with COPD

The data described below reflect exposure to PERFOROMIST Inhalation Solution 20 mcg twice daily by oral inhalation in 586 patients, including 232 exposed for 6 months and 155 exposed for at least 1 year. PERFOROMIST Inhalation Solution was studied in a 12-week, placebo- and active-controlled trial (123 subjects treated with PERFOROMIST Inhalation Solution) and a 52-week, active-controlled trial (463 subjects treated with PERFOROMIST Inhalation Solution). Patients were mostly Caucasians (88%) between 40-90 years old (mean, 64 years old) and had COPD, with a mean FEV1 of 1.33 L. Patients with significant concurrent cardiac and other medical diseases were excluded from the trials.

Table 1 shows adverse reactions from the 12-week, double-blind, placebo-controlled trial where the frequency was greater than or equal to 2% in the PERFOROMIST Inhalation Solution group and where the rate in the PERFOROMIST Inhalation Solution group exceeded the rate in the placebo group. In this trial, the frequency of patients experiencing cardiovascular adverse events was 4.1% for PERFOROMIST Inhalation Solution and 4.4% for placebo. There were no frequently occurring specific cardiovascular adverse events for PERFOROMIST Inhalation Solution (frequency greater than or equal to 1% and greater than placebo). The rate of COPD exacerbations was 4.1% for PERFOROMIST Inhalation Solution and 7.9% for placebo.

TABLE 1
Number of patients with adverse reactions in the 12-week multiple-dose controlled clinical trial
Adverse Reaction | PERFOROMIST Inhalation Solution 20 mcg |  | Placebo
 | n | (%) | n | (%)
Total Patients | 123 | (100) | 114 | (100)
Diarrhea | 6 | (4.9) | 4 | (3.5)
Nausea | 6 | (4.9) | 3 | (2.6)
Nasopharyngitis | 4 | (3.3) | 2 | (1.8)
Dry Mouth | 4 | (3.3) | 2 | (1.8)
Vomiting | 3 | (2.4) | 2 | (1.8)
Dizziness | 3 | (2.4) | 1 | (0.9)
Insomnia | 3 | (2.4) | 0 | 0

Patients treated with PERFOROMIST Inhalation Solution 20 mcg twice daily in the 52-week open-label trial did not experience an increase in specific clinically significant adverse events above the number expected based on the medical condition and age of the patients.

6.3 Postmarketing Experience

The following adverse reactions have been reported during post-approval use of PERFOROMIST Inhalation Solution. Because these reactions are reported voluntarily from a population of uncertain size, it is not always possible to reliably estimate their frequency or establish a causal relationship to drug exposure.

Anaphylactic reactions, urticaria, angioedema (presenting as face, lip, tongue, eye, pharyngeal, or mouth edema), rash, and bronchospasm

7 DRUG INTERACTIONS

7.1 Adrenergic Drugs

If additional adrenergic drugs are to be administered by any route, they should be used with caution because the sympathetic effects of formoterol may be potentiated [see WARNINGS AND PRECAUTIONS (5.3, 5.5, 5.6, 5.7)].

7.2 Xanthine Derivatives, Steroids, or Diuretics

Concomitant treatment with xanthine derivatives, steroids, or diuretics may potentiate any hypokalemic effect of adrenergic agonists [see WARNINGS AND PRECAUTIONS (5.7)].

7.3 Non-potassium Sparing Diuretics

The ECG changes and/or hypokalemia that may result from the administration of non-potassium sparing diuretics (such as loop or thiazide diuretics) can be acutely worsened by beta-agonists, especially when the recommended dose of the beta-agonist is exceeded. Although the clinical significance of these effects is not known, caution is advised in the co-administration of beta-agonists with non-potassium sparing diuretics.

7.4 MAO Inhibitors, Tricyclic Antidepressants, QTc Prolonging Drugs

Formoterol, as with other beta2-agonists, should be administered with extreme caution to patients being treated with monoamine oxidase inhibitors, tricyclic antidepressants, or drugs known to prolong the QTc interval because the effect of adrenergic agonists on the cardiovascular system may be potentiated by these agents. Drugs that are known to prolong the QTc interval have an increased risk of ventricular arrhythmias.

7.5 Beta-blockers

Beta-adrenergic receptor antagonists (beta-blockers) and formoterol may inhibit the effect of each other when administered concurrently. Beta-blockers not only block the therapeutic effects of beta-agonists, but may produce severe bronchospasm in COPD patients. Therefore, patients with COPD should not normally be treated with beta-blockers. However, under certain circumstances, e.g., as prophylaxis after myocardial infarction, there may be no acceptable alternatives to the use of beta-blockers in patients with COPD. In this setting, cardioselective beta-blockers could be considered, although they should be administered with caution.

8 USE IN SPECIFIC POPULATIONS

8.1 Pregnancy

Risk Summary

There are limited available data with PERFOROMIST Inhalation Solution use in pregnant women to inform a drug-associated risk of adverse developmental outcomes. Beta-agonists may interfere with uterine contractility (see Clinical Considerations). In animal reproduction studies, oral administration of formoterol fumarate to pregnant rats and rabbits caused increased fetal malformations (rats and rabbits), decreased fetal weight (rats), and increased neonatal mortality (rats) following administration of doses that produced exposures approximately 730 to 29,000 times the MRHD on a mg/m^2 or AUC basis.These adverse effects generally occurred at large multiples of the MRHD when formoterol fumarate was administered by the oral route to achieve high systemic exposures. No effects were observed in a study with rats that received formoterol fumarate by the inhalation route at an exposure approximately 300 times the MRHD (see Data).

The estimated background risk of major birth defects and miscarriage for the indicated population is unknown. All pregnancies have a background risk of birth defect, loss, or other adverse outcomes. In the U.S. general population, the estimated background risk of major birth defects and miscarriage in clinically recognized pregnancies is 2-4% and 15-20%, respectively.

Clinical Considerations

Labor or delivery

There are no adequate and well-controlled human studies that have studied the effects of PERFOROMIST Inhalation Solution during labor and delivery. Because of the potential for beta-agonists interference with uterine contractility, use of PERFOROMIST Inhalation Solution during labor should be restricted to those patients in whom the benefits clearly outweigh the risk.

Data

Animal Data

In embryofetal development studies with pregnant rats and rabbits dosed throughout the period of organogenesis, formoterol fumarate did not cause malformations in either species. However, for pregnant rats dosed throughout organogenesis, formoterol fumarate caused delayed fetal ossification at an exposure approximately 50 times the MRHD (on a mcg/m^2 basis with maternal oral doses of 200 mcg/kg and higher) and decreased fetal weight at an exposure approximately 1,500 times the MRHD (on a mcg/m^2 basis with maternal oral doses of 6,000 mcg/kg and above). In a pre- and post-natal development study with rats dosed during the late stage of pregnancy, formoterol fumarate caused stillbirth and neonatal mortality at an exposure approximately 1,500 times the MRHD (on a mcg/m^2 basis with maternal oral doses of 6,000 mcg/kg and above). However, no effects were observed in this study at an exposure approximately 50 times the MRHD (on a mcg/m^2 basis with a maternal oral dose of 200 mcg/kg).

In embryofetal development studies, conducted by another testing laboratory, with pregnant rats and rabbits dosed throughout the period of organogenesis, formoterol fumarate was teratogenic in both species. Umbilical hernia, a malformation, was observed in rat fetuses at exposures approximately 730 times the MRHD (on a mcg/m^2 basis with maternal oral doses of 3,000 mcg/kg/day and above). Brachygnathia, a skeletal malformation, was observed in rat fetuses at an exposure approximately 3,600 times the MRHD (on a mcg/m^2 basis with a maternal oral dose of 15,000 mcg/kg/day). In another study with rats, no teratogenic effects were observed with exposures up to approximately 300 times the MRHD (on a mcg/m^2 basis with a maternal inhalation dose of 1,200 mcg/kg/day). Subcapsular cysts on the liver were observed in rabbit fetuses at an exposure approximately 29,000 times the MRHD (on a mcg/m^2 basis with a maternal oral dose of 60,000 mcg/kg/day). No teratogenic effects were observed with exposures up to approximately 1,700 times the MRHD (on a mcg/m^2 basis with a maternal oral dose of 3,500 mcg/kg).

8.2 Lactation

Risk Summary

There are no well-controlled human studies of the use of PERFOROMIST Inhalation Solution in nursing mothers. It is not known whether formoterol fumarate is excreted in human milk, or whether there are effects on the breastfed infant or on the milk production.

In reproductive studies in rats formoterol was excreted in the milk (see Data).

The developmental and health benefits of breastfeeding should be considered along with the mother`s clinical need for PERFOROMIST Inhalation Solution and any potential adverse effects on the breastfed child from PERFOROMIST Inhalation Solution or from the underlying maternal condition.

Data

In a pharmacokinetic study in rats formoterol was excreted in the milk. The amount of radioactive labelled ^3H-formoterol fumarate was less than 2% of that in the maternal plasma.

8.4 Pediatric Use

PERFOROMIST Inhalation Solution is not indicated for use in children. The safety and effectiveness of PERFOROMIST Inhalation Solution in pediatric patients have not been established. The pharmacokinetics of formoterol fumarate has not been studied in pediatric patients.

8.5 Geriatric Use

Of the 586 subjects who received PERFOROMIST Inhalation Solution in clinical studies, 284 were 65 years and over, while 89 were 75 years and over. Of the 123 subjects who received PERFOROMIST Inhalation Solution in the 12-week safety and efficacy trial, 48 (39%) were 65 years of age or older. No overall differences in safety or effectiveness were observed between these subjects and younger subjects. Other reported clinical experience has not identified differences in responses between the elderly and younger adult patients, but greater sensitivity of some older individuals cannot be ruled out.

The pharmacokinetics of PERFOROMIST Inhalation Solution has not been studied in elderly subjects.

10 OVERDOSAGE

The expected signs and symptoms with overdosage of PERFOROMIST Inhalation Solution are those of excessive beta-adrenergic stimulation and/or occurrence or exaggeration of any of the signs and symptoms listed under ADVERSE REACTIONS. Signs and symptoms may include angina, hypertension or hypotension, tachycardia with rates up to 200 beats/min, arrhythmias, nervousness, headache, tremor, seizures, muscle cramps, dry mouth, palpitation, nausea, dizziness, fatigue, malaise, insomnia, hyperglycemia, hypokalemia, and metabolic acidosis. As with all inhaled sympathomimetic medications, cardiac arrest and even death may be associated with an overdose of PERFOROMIST Inhalation Solution.

Treatment of overdosage consists of discontinuation of PERFOROMIST Inhalation Solution together with institution of appropriate symptomatic and/or supportive therapy. The judicious use of a cardioselective beta-receptor blocker may be considered, bearing in mind that such medication can produce bronchospasm. There is insufficient evidence to determine if dialysis is beneficial for overdosage of PERFOROMIST Inhalation Solution. Cardiac monitoring is recommended in cases of overdosage.

For additional information about overdose treatment, call a poison control center (1-800-222-1222).

11 DESCRIPTION

PERFOROMIST (formoterol fumarate) Inhalation Solution is supplied as 2 mL of formoterol fumarate inhalation solution packaged in a 2.5 mL single-use low-density polyethylene vial and overwrapped in a foil pouch. Each vial contains 2 mL of a clear, colorless solution composed of formoterol fumarate dihydrate, USP equivalent to 20 mcg of formoterol fumarate in an isotonic, sterile aqueous solution containing sodium chloride, pH adjusted to 5.0 with citric acid and sodium citrate.

The active component of PERFOROMIST Inhalation Solution is formoterol fumarate dihydrate, USP, a racemate. Formoterol fumarate dihydrate is a beta2-adrenergic bronchodilator. Its chemical name is (±)-2-hydroxy-5-[(1RS)-1-hydroxy-2-[[(1RS)-2-(4-methoxyphenyl)-1-methylethyl]-amino]ethyl]formanilide fumarate dihydrate; its structural formula is:

Formoterol fumarate dihydrate, USP has a molecular weight of 840.92 and its empirical formula is (C19H24N2O4)2•C4H4O4•2H2O. Formoterol fumarate dihydrate, USP is a white to yellowish crystalline powder, which is freely soluble in glacial acetic acid, soluble in methanol, sparingly soluble in ethanol and isopropanol, slightly soluble in water, and practically insoluble in acetone, ethyl acetate, and diethyl ether.

PERFOROMIST Inhalation Solution does not require dilution prior to administration by nebulization. Like all other nebulized treatments, the amount delivered to the lungs will depend on patient factors and the nebulization system used and its performance.

Using the PARI-LC Plus® nebulizer (with a facemask or mouthpiece) connected to a PRONEB® Ultra compressor under in vitro conditions, the mean delivered dose from the mouthpiece was approximately 7.3 mcg (37% of label claim). The mean nebulizer flow rate was 4 LPM and the nebulization time was 9 minutes. PERFOROMIST Inhalation Solution should be administered from a standard jet nebulizer at adequate flow rates via a facemask or mouthpiece.

12 CLINICAL PHARMACOLOGY

12.1 Mechanism of Action

Formoterol fumarate is a long-acting, beta2-adrenergic receptor agonist (beta2-agonist). Inhaled formoterol fumarate acts locally in the lung as a bronchodilator. In vitro studies have shown that formoterol has more than 200-fold greater agonist activity at beta2-receptors than at beta1-receptors. Although beta2-receptors are the predominant adrenergic receptors in bronchial smooth muscle and beta1-receptors are the predominant receptors in the heart, there are also beta2-receptors in the human heart comprising 10% to 50% of the total beta-adrenergic receptors. The precise function of these receptors has not been established, but they raise the possibility that even highly selective beta2-agonists may have cardiac effects.

The pharmacologic effects of beta2-adrenoceptor agonist drugs, including formoterol, are at least in part attributable to stimulation of intracellular adenyl cyclase, the enzyme that catalyzes the conversion of adenosine triphosphate (ATP) to cyclic-3', 5'-adenosine monophosphate (cyclic AMP). Increased cyclic AMP levels cause relaxation of bronchial smooth muscle and inhibition of release of mediators of immediate hypersensitivity from cells, especially from mast cells.

In vitro tests show that formoterol is an inhibitor of the release of mast cell mediators, such as histamine and leukotrienes, from the human lung. Formoterol also inhibits histamine-induced plasma albumin extravasation in anesthetized guinea pigs and inhibits allergen-induced eosinophil influx in dogs with airway hyper-responsiveness. The relevance of these in vitro and animal findings to humans with COPD is unknown.

12.2 Pharmacodynamics

Systemic Safety and Pharmacokinetic / Pharmacodynamic Relationships

The major adverse effects of inhaled beta2-agonists occur as a result of excessive activation of the systemic beta-adrenergic receptors. The most common adverse effects in adults include skeletal muscle tremor and cramps, insomnia, tachycardia, decreases in plasma potassium, and increases in plasma glucose.

Changes in serum potassium and serum glucose were evaluated in 12 COPD patients following inhalation of single doses of PERFOROMIST Inhalation Solution containing 10, 20 and 244 mcg of formoterol fumarate (calculated on an anhydrous basis) in a crossover study. At 1 hour after treatment with formoterol fumarate inhalation solution, mean (± standard deviation) serum glucose rose 26 ± 30, 29 ± 28, and 38 ± 44 mg/dL, respectively, and was not significantly different from baseline or trough level at 24 hours post-dose. At 1 hour after dosing with formoterol fumarate inhalation solution 244 mcg, serum potassium fell by 0.68 ± 0.4 mEq/L, and was not different from baseline or trough level at 24 hours post-dose.

Linear pharmacokinetic/pharmacodynamic (PK/PD) relationships between urinary formoterol excretion and decreases in serum potassium, increases in plasma glucose, and increases in heart rate were generally observed with another inhalation formulation of formoterol fumarate and hence would be expected with PERFOROMIST Inhalation Solution also. Following single dose administration of 10-fold the recommended clinical dose of the other formoterol fumarate inhalation formulation having comparable exposure to single dose of 244 mcg of PERFOROMIST Inhalation Solution (approximately 12-fold the recommended clinical dose) in healthy subjects, the formoterol plasma concentration was found to be highly correlated with the reduction in plasma potassium concentration. Data from this study showed that maximum reductions from baseline in plasma potassium ranged from 0.55 to 1.52 mmol/L with a median maximum reduction of 1.01 mmol/L. Generally, the maximum effect on plasma potassium was noted 1 to 3 hours after peak formoterol plasma concentrations were achieved.

Electrophysiology

In the dose-ranging study of PERFOROMIST Inhalation Solution, ECG-determined heart rate increased by a mean of 6 ±3 beats per minute at 6 hours after a single dose of 244 mcg, but was back to predose level at 16-24 hours.

The effect of PERFOROMIST Inhalation Solution on heart rate and cardiac rhythm was studied in a 12-week clinical trial comparing PERFOROMIST Inhalation Solution to placebo and an active control treatment. COPD patients, including 105 patients exposed to PERFOROMIST Inhalation Solution, underwent continuous electrocardiographic (Holter) monitoring during two 24-hour periods (study baseline and after 8-12 weeks of treatment). ECGs were performed pre-dose and at 2 to 3 hours post-dose at study baseline (prior to dosing) and after 4, 8 and 12 weeks of treatment. Bazett’s and Fridericia’s methods were used to correct the QT interval for heart rate (QTcB and QTcF, respectively). The mean increase from baseline in QTcB interval over the 12-week treatment period was ≤ 4.8 msec for PERFOROMIST Inhalation Solution and ≤ 4.6 msec for placebo. The percent of patients who experienced a maximum change in QTc greater than 60 msec at any time during the 12-week treatment period was 0% and 1.8% for PERFOROMIST Inhalation Solution and placebo, respectively, based on Bazett’s correction, and 1.6% and 0.9%, respectively, based on Fridericia’s correction. Prolonged QT was reported as an adverse event in 1 (0.8%) patient treated with PERFOROMIST Inhalation Solution and 2 (1.8%) placebo patients. No occurrences of atrial fibrillation or ventricular tachycardia were observed during 24-hour Holter monitoring or reported as adverse events in patients treated with PERFOROMIST Inhalation Solution after the start of dosing. No increase in supraventricular tachycardia over placebo-treated subjects was observed. The mean increase in maximum heart rate from baseline to 8-12 weeks after the start of dosing was 0.6 beats per minute (bpm) for patients treated with PERFOROMIST Inhalation Solution twice daily compared to 1.2 bpm for placebo patients. There were no clinically meaningful differences from placebo in acute or chronic effects on heart rate, including QTcB and QTcF, or cardiac rhythm resulting from treatment with PERFOROMIST Inhalation Solution.

At an exposure from formoterol fumarate dry powder formulation comparable to approximately 12-fold the recommended dose of PERFOROMIST Inhalation Solution, a mean maximum increase of pulse rate of 26 bpm was observed 6 hours post dose in healthy subjects. This study showed that the maximum increase of mean corrected QT interval (QTc) was 25 msec when calculated using Bazett's correction and was 8 msec when calculated using Fridericia's correction. The QTc returned to baseline within 12 to 24 hours post-dose. Formoterol plasma concentrations were weakly correlated with pulse rate and increase of QTc duration. The effects on pulse rate and QTc interval are known pharmacological effects of this class of study drug and were not unexpected at this supratherapeutic formoterol fumarate inhalation dose.

Tachyphylaxis / Tolerance

Tolerance to the effects of inhaled beta-agonists can occur with regularly-scheduled, chronic use. In a placebo-controlled clinical trial in 351 adult patients with COPD, the bronchodilating effect of PERFOROMIST Inhalation Solution was determined by the FEV1 area under the curve over 12 hours following dosing on Day 1 and after 12 weeks of treatment. The effect of PERFOROMIST Inhalation Solution did not decrease after 12 weeks of twice-daily treatment (Figures 1 and 2).

12.3 Pharmacokinetics

Information on the pharmacokinetics of formoterol (dry powder and/or inhalation solution) in plasma and/or urine is available in healthy subjects as well as patients with chronic obstructive pulmonary disease after oral inhalation of doses at and above the therapeutic dose.

Urinary excretion of unchanged formoterol was used as an indirect measure of systemic exposure. Plasma drug disposition data parallel urinary excretion, and the elimination half-lives calculated for urine and plasma are similar.

Absorption

Pharmacokinetic properties of formoterol fumarate were evaluated in 12 COPD patients following inhalation of single doses of PERFOROMIST Inhalation Solution containing 10, 20 and 244 mcg of formoterol fumarate (calculated on an anhydrous basis) and 12 mcg formoterol fumarate dry powder, through 36 hours after single-dose administration. Formoterol fumarate concentrations in plasma following the 10 and 20 mcg doses of PERFOROMIST Inhalation Solution and the 12 mcg dose of formoterol fumarate dry powder were undetectable or only detected sporadically at very low concentrations. Following a single 244 mcg dose of PERFOROMIST Inhalation Solution (approximately 12 times the recommended clinical dose), formoterol fumarate concentrations were readily measurable in plasma, exhibiting rapid absorption into plasma, and reaching a maximum drug concentration of 72 pg/mL within approximately 12 minutes of dosing.

The mean amount of formoterol excreted unchanged in 24-hour urine following single oral inhalation doses of 10, 20, and 244 mcg PERFOROMIST Inhalation Solution were found to be 109.7 ng, 349.6 ng, and 3317.5 ng, respectively. These findings indicate a near dose proportional increase in systemic exposure within the dose range tested.

When 12 mcg of a dry powder formulation of formoterol fumarate was given twice daily to COPD patients by oral inhalation for 12 weeks, the accumulation index, based on the urinary excretion of unchanged formoterol was 1.19 to 1.38. This suggests some accumulation of formoterol in plasma with multiple dosing. Although multiple-dose pharmacokinetic data is unavailable from PERFOROMIST Inhalation Solution, assumption of linear pharmacokinetics allows a reasonable prediction of minimal accumulation based on single-dose pharmacokinetics. As with many drug products for oral inhalation, it is likely that the majority of the inhaled formoterol fumarate delivered is swallowed and then absorbed from the gastrointestinal tract.

Distribution

The binding of formoterol to human plasma proteins in vitro was 61% to 64% at concentrations from 0.1 to 100 ng/mL. Binding to human serum albumin in vitro was 31% to 38% over a range of 5 to 500 ng/mL. The concentrations of formoterol used to assess the plasma protein binding were higher than those achieved in plasma following inhalation of a single 244 mcg dose of PERFOROMIST Inhalation Solution.

Metabolism

Formoterol is metabolized primarily by direct glucuronidation at either the phenolic or aliphatic hydroxyl group and O-demethylation followed by glucuronide conjugation at either phenolic hydroxyl groups. Minor pathways involve sulfate conjugation of formoterol and deformylation followed by sulfate conjugation. The most prominent pathway involves direct conjugation at the phenolic hydroxyl group. The second major pathway involves O-demethylation followed by conjugation at the phenolic 2'-hydroxyl group. In vitro studies showed that multiple drug-metabolizing enzymes catalyze glucuronidation (UGT1A1, 1A8, 1A9, 2B7 and 2B15 were the most predominant enzymes) and O-demethylation (CYP2D6, CYP2C19, CYP2C9 and CYP2A6) of formoterol. Formoterol did not inhibit CYP450 enzymes at therapeutically relevant concentrations. Some patients may be deficient in CYP2D6 or 2C19 or both. Whether a deficiency in one or both of these isozymes results in elevated systemic exposure to formoterol or systemic adverse effects has not been adequately explored.

Excretion

Following administration of single 10, 20, and 244 mcg PERFOROMIST Inhalation Solution doses (calculated on an anhydrous basis) delivered via nebulizer in 12 COPD patients, on average, about 1.1% to 1.7% of the dose was excreted in the urine as unchanged formoterol as compared to about 3.4% excreted unchanged following inhalation administration of 12 mcg of formoterol fumarate dry powder. Renal clearance of formoterol following inhalation administration of PERFOROMIST Inhalation Solution in these subjects was about 157 mL/min. Based on plasma concentrations measured following the 244 mcg dose, the mean terminal elimination half-life was determined to be 7 hours.

Gender

As reported for another formoterol fumarate inhalation formulation, upon correction for body weight, pharmacokinetics of formoterol fumarate did not differ significantly between males and females.

Geriatric, Pediatric, Hepatic/Renal Impairment

The pharmacokinetics of formoterol fumarate has not been studied in elderly and pediatric patient populations. The pharmacokinetics of formoterol fumarate has not been studied in subjects with hepatic or renal impairment.

13 NONCLINICAL TOXICOLOGY

13.1 Carcinogenesis, Mutagenesis, Impairment of Fertility

The carcinogenic potential of formoterol fumarate has been evaluated in 2-year drinking water and dietary studies in both rats and mice. In rats, the incidence of ovarian leiomyomas was increased at doses of 15,000 mcg/kg and above in the drinking water study and at 20,000 mcg/kg in the dietary study (AUC exposure approximately 2,300 times human exposure at the maximum recommended daily inhalation dose), but not at dietary doses up to 5,000 mcg/kg (AUC exposure approximately 570 times human exposure at the maximum recommended daily inhalation dose). In the dietary study, the incidence of benign ovarian theca-cell tumors was increased at doses of 500 mcg/kg (AUC exposure was approximately 57 times human exposure at the maximum recommended daily inhalation dose) and above. This finding was not observed in the drinking water study, nor was it seen in mice (see below).

In mice, the incidence of adrenal subcapsular adenomas and carcinomas was increased in males at doses of 69,000 mcg/kg (AUC exposure approximately 1000 times human exposure at the maximum recommended daily inhalation dose) and above in the drinking water study, but not at doses up to 50,000 mcg/kg (AUC exposure approximately 750 times human exposure at the maximum recommended daily inhalation dose) in the dietary study. The incidence of hepatocarcinomas was increased in the dietary study at doses of 20,000 and 50,000 mcg/kg in females (AUC exposures approximately 300 and 750 times human exposure at the maximum recommended daily inhalation dose, respectively) and 50,000 mcg/kg in males, but not at doses up to 5,000 mcg/kg (AUC exposure approximately 75 times human exposure at the maximum recommended daily inhalation dose). Also in the dietary study, the incidence of uterine leiomyomas and leiomyosarcomas was increased at doses of 2,000 mcg/kg (AUC exposure was approximately 30 times human exposure at the maximum recommended daily inhalation dose) and above. Increases in leiomyomas of the rodent female genital tract have been similarly demonstrated with other beta-agonist drugs.

Formoterol fumarate was not mutagenic or clastogenic in the following tests: mutagenicity tests in bacterial and mammalian cells, chromosomal analyses in mammalian cells, unscheduled DNA synthesis repair tests in rat hepatocytes and human fibroblasts, transformation assay in mammalian fibroblasts and micronucleus tests in mice and rats.

Reproduction studies in rats revealed no impairment of fertility at oral doses up to 3,000 mcg/kg (approximately 730 times the maximum recommended daily inhalation powder dose in humans on a mcg/m^2 basis).

13.2 Animal Pharmacology

Studies in laboratory animals (minipigs, rodents, and dogs) have demonstrated the occurrence of cardiac arrhythmias and sudden death (with histologic evidence of myocardial necrosis) when beta-agonists and methylxanthines are administered concurrently. The clinical significance of these findings is unknown [see DRUG INTERACTIONS, Xanthine Derivatives, Steroids, or Diuretics (7.2)].

14 CLINICAL STUDIES

14.1 Adult COPD Trial

PERFOROMIST (formoterol fumarate) Inhalation Solution was evaluated in a 12-week, double-blind, placebo- and active-controlled, randomized, parallel-group, multicenter trial conducted in the United States. Of a total enrollment of 351 adults (age range: 40 to 86 years; mean age: 63 years) with COPD who had a mean pre-bronchodilator FEV1 of 1.34 liters (44% of predicted), 237 patients were randomized to PERFOROMIST Inhalation Solution 20 mcg or placebo, administered twice daily via a PARI-LC Plus® nebulizer with a PRONEB® Ultra compressor. The diagnosis of COPD was based upon a prior clinical diagnosis of COPD, a smoking history (at least 10 pack-years), age (at least 40 years), and spirometry results (pre-bronchodilator baseline FEV1 at least 30% and less than 70% of the predicted value, and the FEV1/FVC less than 70%). About 58% of patients had bronchodilator reversibility, defined as a 10% or greater increase in FEV1 after inhalation of 2 actuations (180 mcg) of albuterol from a metered dose inhaler. About 86% (106) of patients treated with PERFOROMIST Inhalation Solution and 74% (84) of placebo patients completed the trial.

PERFOROMIST Inhalation Solution 20 mcg twice daily resulted in significantly greater post-dose bronchodilation (as measured by serial FEV1 for 12 hours post-dose; the primary efficacy analysis) compared to placebo when evaluated at endpoint (week 12 for completers and last observation for dropouts). Similar results were seen on Day 1 and at subsequent timepoints during the trial.

Mean FEV1 measurements at Day 1 (Figure 1) and at endpoint (Figure 2) are shown below.

Figure 1 Mean* FEV1 at Day 1

Figure 2 Mean* FEV1 at Endpoint after 12 Weeks of Treatment

* Figures show least-squares means adjusted for baseline FEV1

Patients treated with PERFOROMIST Inhalation Solution used less rescue albuterol during the trial compared to patients treated with placebo.

Examination of age (≥ 65 or younger) and gender subgroups did not identify differences in response to PERFOROMIST Inhalation Solution. There were too few non-Caucasian subjects to assess differences in populations defined by race adequately.

In the 12-week study, 78% of subjects achieved a 15% increase from baseline FEV1 following the first dose of PERFOROMIST Inhalation Solution 20 mcg. In these subjects, the median time to onset of bronchodilation, defined as 15% increase in FEV1, was 11.7 minutes. When defined as an increase in FEV1 of 12% and 200 mL, the time to onset of bronchodilation was 13.1 minutes after dosing. The median time to peak bronchodilator effect was 2 hours after dosing.

16 HOW SUPPLIED/STORAGE AND HANDLING

PERFOROMIST (formoterol fumarate) Inhalation Solution is supplied as a 2 mL sterile solution for nebulization in 2.5 mL low-density polyethylene unit dose vials. Each vial is overwrapped in a foil pouch and supplied in cartons as listed below.

Carton of 30 individually wrapped unit dose vials, NDC 49502-605-30

Carton of 60 individually wrapped unit dose vials, NDC 49502-605-61

Storage and Handling:

Prior to dispensing to the patient: Store in a refrigerator, 2°C to 8°C (36°F to 46°F). Protect pouch from light and heat.

After dispensing to the patient: Store in a refrigerator at 2°C to 8°C (36°F to 46°F) and discard when drug expires or store at room temperature, 20°C to 25°C (68°F to 77°F) and discard if not used after 3 months. Protect pouch from light and heat.

- PERFOROMIST Inhalation Solution should only be administered via a standard jet nebulizer connected to an air compressor with an adequate airflow and equipped with a facemask or mouthpiece.
- Vial should always be stored in the foil pouch, and only removed IMMEDIATELY before use.
- Do not take by mouth.
- Contents of any partially used container should be discarded.
- Discard the container and top after use.
- Keep out of the reach of children

17 PATIENT COUNSELING INFORMATION

Advise the patient to read the FDA-approved patient labeling (Patient Information and Instructions for Use).

Serious Asthma-Related Events

Inform patients that long-acting beta agonist, such as PERFOROMIST, when used as monotherapy [without an inhaled corticosteroid], increase the risk of serious asthma-related events, including asthma-related death. PERFOROMIST is not indicated for the treatment of asthma.

Acute Exacerbations or Deteriorations

PERFOROMIST Inhalation Solution is not indicated for relief of acute symptoms, and extra doses should not be used for that purpose. Acute symptoms should be treated with an inhaled, short-acting beta2-agonist (the healthcare provider should provide the patient with such medication and instruct the patient in how it should be used). Patients should be instructed to seek medical attention if their symptoms worsen despite recommended doses of PERFOROMIST Inhalation Solution, if PERFOROMIST Inhalation Solution treatment becomes less effective, or if they need more inhalations of a short-acting beta2-agonist than usual.

Appropriate Dosing

Patients should not stop using PERFOROMIST Inhalation Solution unless told to do so by a healthcare provider because symptoms may get worse. Patients should not inhale more than the prescribed number of vials at any one time. The daily dosage of PERFOROMIST Inhalation Solution should not exceed one vial twice daily (40 mcg total daily dose). Excessive use of sympathomimetics may cause significant cardiovascular effects and may be fatal.

Concomitant Therapy

Patients who have been taking inhaled, short-acting beta2-agonists (e.g., albuterol) on a regular basis should be instructed to discontinue the regular use of these products and use them only for symptomatic relief of acute symptoms. PERFOROMIST Inhalation Solution should not be used in conjunction with other inhaled medications containing long-acting beta2-agonists. Patients should be warned not to stop or change the dose of other concomitant COPD therapy without medical advice, even if symptoms improve after initiating treatment with PERFOROMIST Inhalation Solution.

Common Adverse Reactions with Beta2-agonists

Patients should be informed that treatment with beta2-agonists may lead to adverse reactions that include palpitations, chest pain, rapid heart rate, increased or decreased blood pressure, headache, tremor, nervousness, dry mouth, muscle cramps, nausea, dizziness, fatigue, malaise, low blood potassium, high blood sugar, high blood acid, or trouble sleeping [see ADVERSE REACTIONS (6.1)].

Instructions for Administration

It is important that patients understand how to use PERFOROMIST Inhalation Solution with a nebulizer appropriately [see the accompanying Patient Information]. Patients should be instructed not to mix other medications with PERFOROMIST Inhalation Solution or ingest PERFOROMIST Inhalation Solution. Patients should throw the plastic dispensing container away immediately after use. Due to their small size, the container and top pose a danger of choking to young children.

Manufactured for:
Mylan Specialty L.P.
Morgantown, WV 26505 U.S.A.

Manufactured by:
The Ritedose Corporation
Columbia, SC 29203 U.S.A.

U.S. Pat. No. 6,667,344
U.S. Pat. No. 6,814,953
U.S. Pat. No. 7,348,362
U.S. Pat. No. 7,462,645
U.S. Pat. No. 8,623,922
U.S. Pat. No. 9,730,890

FORMIS:R3

The brands listed are trademarks of their respective owners.

PATIENT INFORMATION

PERFOROMIST® (Per-FOR-o-mist)

(formoterol fumarate) Inhalation Solution

What is PERFOROMIST Inhalation Solution?

- PERFOROMIST Inhalation Solution is a long-acting beta2 adrenergic agonist (LABA) used to control the symptoms of COPD in adults with COPD. COPD is a chronic lung disease that includes chronic bronchitis, emphysema, or both.
- PERFOROMIST Inhalation Solution is only for use with a nebulizer.
- LABA medicines such as PERFOROMIST Inhalation Solution help the muscles around the airways in your lungs stay relaxed to prevent symptoms, such as wheezing, cough, chest tightness, and shortness of breath.
- PERFOROMIST Inhalation Solution is for long-term use and should be taken 2 times each day, to improve the symptoms of COPD for better breathing.
- PERFOROMIST Inhalation Solution is not used to treat sudden symptoms of COPD.
- PERFOROMIST is not for the treatment of asthma. It is not known if PERFOROMIST Inhalation Solution is safe and effective in people with asthma.
- PERFOROMIST Inhalation Solution should not be used in children. It is not known if PERFOROMIST Inhalation Solution is safe and effective in children.

- Do not use PERFOROMIST Inhalation Solution if you have asthma.

Before using PERFOROMIST Inhalation Solution tell your healthcare provider about all of your medical conditions, including if you:

- have heart problems
- have high blood pressure
- have diabetes
- have seizures
- have thyroid problems
- have liver problems
- are pregnant or plan to become pregnant. It is not known if the medicine formoterol in PERFOROMIST Inhalation Solution passes into breast milk and if it can harm your baby.
- are breastfeeding or plan to breastfeed. It is not known if the medicine formoterol in PERFOROMIST Inhalation Solution passes into breast milk and if it can harm your baby.

Tell your healthcare provider about all the medicines you take including prescription and over-the-counter medicines, vitamins and herbal supplements. PERFOROMIST Inhalation Solution and certain other medicines may interact with each other. This may cause serious side effects.

Know the medicines you take. Keep a list of them to show your healthcare provider and pharmacist each time you get a new medicine.

How should I use PERFOROMIST Inhalation Solution?

Read the step-by-step instructions for using PERFOROMIST Inhalation Solution at the end of this Patient Information leaflet.

- Use PERFOROMIST Inhalation Solution exactly as prescribed. One unit dose vial of PERFOROMIST Inhalation Solution is one dose. The usual dose of PERFOROMIST Inhalation Solution is 1 unit dose vial, 2 times each day (morning and evening) breathed in through your nebulizer machine. The 2 doses should be about 12 hours apart. Do not use more than 2 vials of PERFOROMIST Inhalation Solution a day.
- Do not mix other medicines with PERFOROMIST Inhalation Solution in your nebulizer machine.
- If you miss a dose of PERFOROMIST Inhalation Solution, just skip that dose. Take your next dose at your usual time. Do not take 2 doses at one time.
- While you are using PERFOROMIST Inhalation Solution 2 times each day:
  - do not use other medicines that contain a long-acting beta2-agonist (LABA) for any reason.
  - do not use your short-acting beta2-agonist medicine on regular basis (four times a day).
- PERFOROMIST Inhalation Solution does not relieve sudden symptoms of COPD. Always have a rescue inhaler medicine with you to treat sudden symptoms. If you do not have a rescue inhaler medicine, call your healthcare provider to have one prescribed for you.
- Do not stop using PERFOROMIST Inhalation Solution or other medicines to control or treat your COPD unless told to do so by your healthcare provider because your symptoms might get worse. Your healthcare provider will change your medicines as needed.
- Do not use PERFOROMIST Inhalation Solution:
  - more often than prescribed,
  - more medicine than prescribed for you, or
  - with other LABA medicines
  Call your healthcare provider or get emergency medical care right away if your breathing problems worsen with PERFOROMIST Inhalation Solution, you need to use your rescue medicine more often than usual, or your rescue medicine does not work as well for you to relieve your symptoms.

What are the possible side effects of PERFOROMIST Inhalation Solution?

PERFOROMIST Inhalation Solution can cause serious side effects, including:

- people with asthma who take long-acting beta2 adrenergic agonist (LABA) medicines, such as PERFOROMIST Inhalation Solution, without also using a medicine called an inhaled corticosteroid, have an increased risk of serious problems from asthma, including being hospitalized, needing a tube placed in their airway to help them breathe, or death.
  - Call your healthcare provider if breathing problems worsen over time while using PERFOROMIST Inhalation Solution. You may need a different treatment.
  - Get emergency medical care if:
    - breathing problems worsen quickly
    - you use your rescue inhaler medicine, but it does not relieve your breathing problems
- COPD symptoms that get worse over time. If your COPD symptoms worsen over time, do not increase your dose of PEFOROMIST Inhalation Solution, instead call your healthcare provider.
- using too much of a LABA medicine may cause:

- chest pain
- fast and irregular heartbeat
- tremor

- increased blood pressure
- headache
- nervousness

- sudden shortness of breath immediately after use of PERFOROMIST Inhalation Solution. Sudden shortness of breath may be life-threatening. If you have sudden breathing problems immediately after inhaling your medicine, call your healthcare provider or go to nearest hospital emergency room right away.
- effects on your heart, including fast or irregular heartbeat, chest pain or increased blood pressure.
- changes in laboratory levels, including high levels of blood sugar (hyperglycemia) and low levels of potassium (hypokalemia), which may cause symptoms of muscle spasm, muscle weakness or abnormal heart rhythm.
- serious allergic reactions including rash, hives, swelling of the face, mouth, and tongue, and breathing problems. Call your healthcare provider or get emergency medical care if you get any symptoms of a serious allergic reaction.

Common side effects of PERFOROMIST Inhalation Solution include:

- headache
- muscle cramps
- dizziness

- tremor
- nausea
- tiredness

- nervousness
- vomiting
- trouble sleeping

- dry mouth
- diarrhea

Tell your healthcare provider if you get any side effect that bothers you or that does not go away.

These are not all the possible side effects of PERFOROMIST Inhalation Solution. For more information, ask your healthcare provider or pharmacist for more information.

Call your doctor for medical advice about side effects. You may report side effects to FDA at 1-800-FDA-1088.

How should I store PERFOROMIST Inhalation Solution?

- Store PERFOROMIST Inhalation Solution in a refrigerator between 36° to 46°F (2° to 8°C) in the protective foil pouch. Protect from light and heat. Do not open a sealed pouch until you are ready to use a dose of PERFOROMIST Inhalation Solution. After a sealed pouch is opened, PERFOROMIST Inhalation Solution must be used right away. PERFOROMIST Inhalation Solution may be used directly from the refrigerator.
- PERFOROMIST Inhalation Solution may also be stored at room temperature between 68ºF to 77ºF (20º to 25ºC) for up to 3 months (90 days). If stored at room temperature, discard PERFOROMIST Inhalation Solution if it is not used after 3 months or if past the expiration date, whichever is sooner. Space is provided on the packaging to record dispense date and use by date.
- Do not use PERFOROMIST Inhalation Solution after the expiration date provided on the foil pouch and vial.
- PERFOROMIST Inhalation Solution should be colorless. Discard PERFOROMIST Inhalation Solution if it is not colorless.

Keep PERFOROMIST Inhalation Solution and all medicines out of the reach of children.

General information about the safe and effective use of PERFOROMIST Inhalation Solution.

Medicines are sometimes prescribed for purposes that are not listed in a Patient Information leaflet. Do not use PERFOROMIST Inhalation Solution for a condition for which it was not prescribed. Do not give PERFOROMIST Inhalation Solution to other people, even if they have the same symptoms that you have. It may harm them.

You can ask your health care provider or pharmacist for information about PERFOROMIST Inhalation Solution that is written for health professionals.

What are the ingredients in PERFOROMIST Inhalation Solution?

Active ingredient: formoterol

Inactive ingredients: sodium chloride, citric acid and sodium citrate

Manufactured for: Mylan Specialty L.P., Morgantown, WV 26505 U.S.A.

Manufactured by: The Ritedose Corporation, Columbia, SC 29203 U.S.A.

Perforomist® is a registered trademark of Mylan Specialty L.P.

For more information, call Mylan at 1-877-446-3679 (1-877-4-INFO-RX).

This Patient Information has been approved by the U.S. Food and Drug Administration Issued: 5/2019 PIL:FORMIS:R1

Instructions for Using PERFOROMIST (formoterol fumarate) Inhalation Solution

PERFOROMIST Inhalation Solution is used only in a standard jet nebulizer machine connected to an air compressor. Make sure you know how to use your nebulizer machine before you use it to breathe in PERFOROMIST Inhalation Solution or other medicines.

Do not mix PERFOROMIST Inhalation Solution with other medicines in your nebulizer machine.

PERFOROMIST Inhalation Solution comes sealed in a foil pouch. Do not open a sealed pouch until you are ready to use a dose of PERFOROMIST Inhalation Solution.

1. Remove vial from the foil pouch.
2. Twist the cap completely off the vial and squeeze all the medicine into the nebulizer medicine cup (reservoir) (Figure 1).
3. Connect the nebulizer reservoir to the mouthpiece or facemask (Figure 2).
4. Connect the nebulizer to the compressor.
5. Sit in a comfortable, upright position. Place the mouthpiece in your mouth (Figure 3) or put on the facemask (Figure 4); and turn on the compressor.
6. Breathe as calmly, deeply and evenly as possible through your mouth until no more mist is formed in the nebulizer reservoir. The average nebulization time is 9 minutes. At this point, the treatment is finished.
7. Discard the PERFOROMIST Inhalation Solution container and top after use.
8. Clean the nebulizer (see manufacturer’s instructions).

Manufactured for:
Mylan Specialty L.P.
Morgantown, WV 26505 U.S.A.

Manufactured by:
The Ritedose Corporation
Columbia, SC 29203 U.S.A.

This Instructions for Use has been approved by the U.S. Food and Drug Administration

Revised: 5/2019
IFU:FORMIS:R1

PRINCIPAL DISPLAY PANEL – 20 mcg/2 mL

NDC 49502-605-30

Perforomist®
(formoterol fumarate) INHALATION SOLUTION
20 mcg/2 mL vial

Patient Information for Patients Enclosed

Sterile Unit Dose Vials - Individually Wrapped - For Oral Inhalation Only

EACH 2 mL VIAL CONTAINS: ACTIVE: Formoterol fumarate, USP.

INACTIVES: Citric acid, sodium citrate, sodium chloride, and water.

CARTON CONTAINS: 30 individually wrapped 2 mL vials

Discard three months
after dispense date.
Use by: ________

STORAGE CONDITIONS:

PRIOR TO DISPENSING TO THE PATIENT: Store refrigerated, 2°C to 8°C (36°F to 46°F). Protect pouch from light and heat.

AFTER DISPENSING TO THE PATIENT: Store in a refrigerator at 2°C to 8°C (36°F to 46°F) and discard when drug expires or store at room temperature, 20°C to 25°C (68°F to 77°F) and discard if not used after 3 months. Protect pouch from light and heat.

VIAL SHOULD ALWAYS BE STORED IN THE FOIL POUCH, AND ONLY REMOVED IMMEDIATELY BEFORE USE.

Keep out of reach of children.

FOR THE HEALTHCARE PROVIDER: When Perforomist® Inhalation Solution is
dispensed to the patient, inform the patient to discard the product at the
expiration date on the product if storing in a refrigerator or if the patient plans
on storing the drug at room temperature, write an expiration date in the “Use
by” box on the carton or dispensing container. The “Use by” date should not
exceed 3 months from date dispensed. Protect pouch from light and heat.

FOR THE PATIENT: Use Perforomist® Inhalation Solution prior to the
“Use by” date if stored at room temperature; otherwise, discard when
the product expires.

Rx only

Manufactured for:
Mylan Specialty L.P.
Morgantown, WV 26505 U.S.A.

Manufactured by:
The Ritedose Corporation
Columbia, SC 29203 U.S.A.

U.S. Pat. Nos. 6,667,344, 6,814,953, 7,348,362, 7,462,645, 8,623,922, and 9,730,890

Mylan Specialty L.P., Morgantown, WV 26505

MS:605:30C:R3 RPSC0340